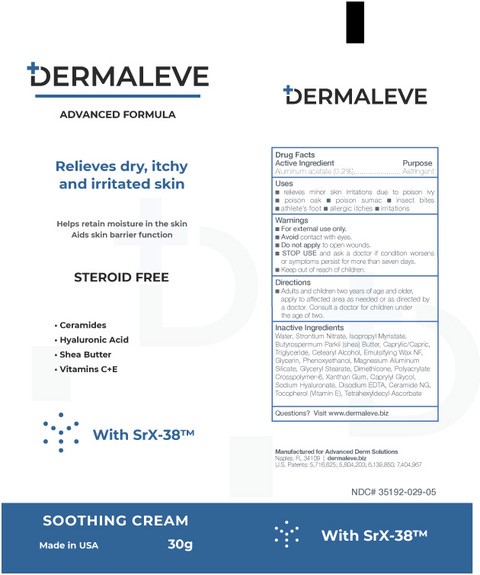 DRUG LABEL: Skin protectant
NDC: 35192-029 | Form: CREAM
Manufacturer: CA-Botana International
Category: otc | Type: HUMAN OTC DRUG LABEL
Date: 20231016

ACTIVE INGREDIENTS: ALUMINUM ACETATE 0.2 g/30 g
INACTIVE INGREDIENTS: XANTHAN GUM; CAPRYLYL GLYCOL; CERAMIDE NG; WATER O-18; MAGNESIUM ALUMINUM SILICATE TYPE IA; GLYCERYL STEARATE SE; EDETATE DISODIUM; TOCOPHEROL; TETRAHEXYLDECYL ASCORBATE; SHEA BUTTER; PHENOXYETHANOL; STRONTIUM NITRATE; ISOPROPYL MYRISTATE; CAPRYLIC/CAPRIC MONO/DI-GLYCERIDES; CETYL ALCOHOL; DIMETHICONE 100; POLYACRYLIC ACID (450000 MW); HYALURONIC ACID; STEARYL ALCOHOL; POLAWAX POLYSORBATE; GLYCERIN

Dermaleve skin protectant

INACTIVE INGREDIENT

Cetyl Alcohol, Dimethico 100, Polyacrylic Acid, Polawax Polysorbate, Glycerin, Caprylyl Glycol, Ceramide NG, Water, Magnesium Aluminum Silicate, Glyceryl Stearate, Edenate Disodium, Tocopherol, Tetrahexyldecyl Ascorbate, Shea Butter, Phenoxyethanol, Strontium Nitrate, Xanthan Gum Hyaloronic acid, Stearyl Alcohol, IsopropyylMyrristate, Caprylic/Capric Tryglyceride

DOSAGE AND ADMINISTRATION

use 3 times to[pically

Keep out of reach of children

INDICATIONS AND USAGE

For external use only Avoid contact with eyes Do not apply to open wound Stop use and ask a doctor if condition worsens or symtomps persist for more than seven days Keep out reach of children